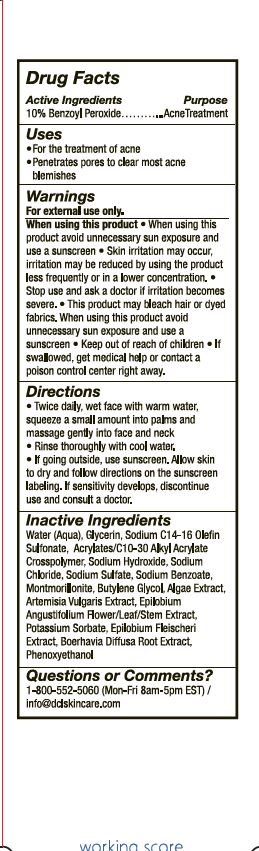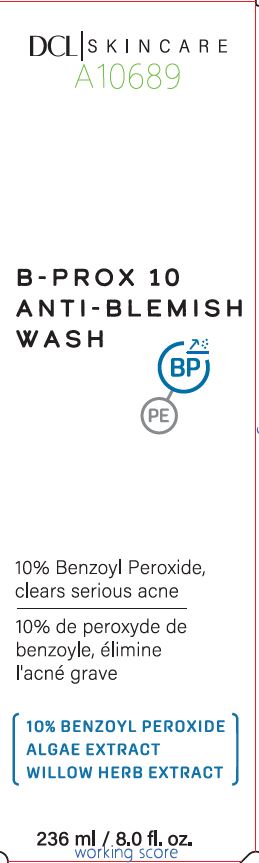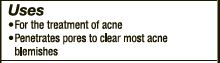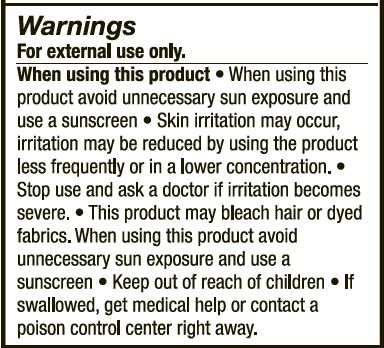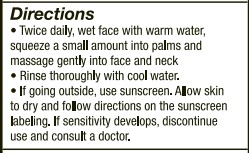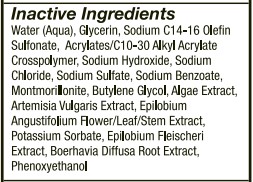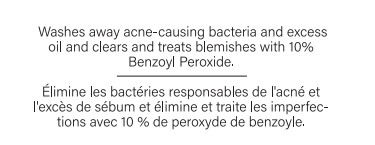 DRUG LABEL: Milbar Laboratories
NDC: 57577-531 | Form: RINSE
Manufacturer: Milbar Laboratories
Category: otc | Type: HUMAN OTC DRUG LABEL
Date: 20240405

ACTIVE INGREDIENTS: BENZOYL PEROXIDE 24.3 g/236 mL
INACTIVE INGREDIENTS: WATER; GLYCERIN; BUTYLENE GLYCOL; PROPANEDIOL; ARTEMISIA VULGARIS TOP OIL; SODIUM C14-16 OLEFIN SULFONATE; CITRIC ACID MONOHYDRATE; SODIUM CITRATE; CARBOMER HOMOPOLYMER, UNSPECIFIED TYPE; DI-2-HEXYL SODIUM SULFOSUCCINATE; POTASSIUM SORBATE; SODIUM CHLORIDE; SODIUM BENZOATE; SODIUM METABISULFITE; BOERHAVIA DIFFUSA ROOT; SODIUM HYDROXIDE; ACRYLATES/C10-30 ALKYL ACRYLATE CROSSPOLYMER (60000 MPA.S AT 0.5%); LAMINARIA DIGITATA; EPILOBIUM ANGUSTIFOLIUM WHOLE; SODIUM SULFATE; EPILOBIUM FLEISCHERI WHOLE; PHENOXYETHANOL

WARNINGS

Warning Section

Uses

Active Ingredient Section